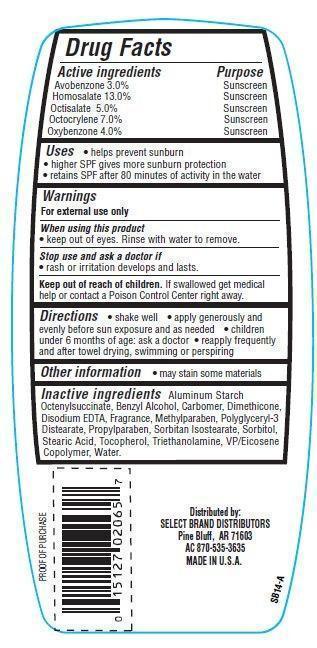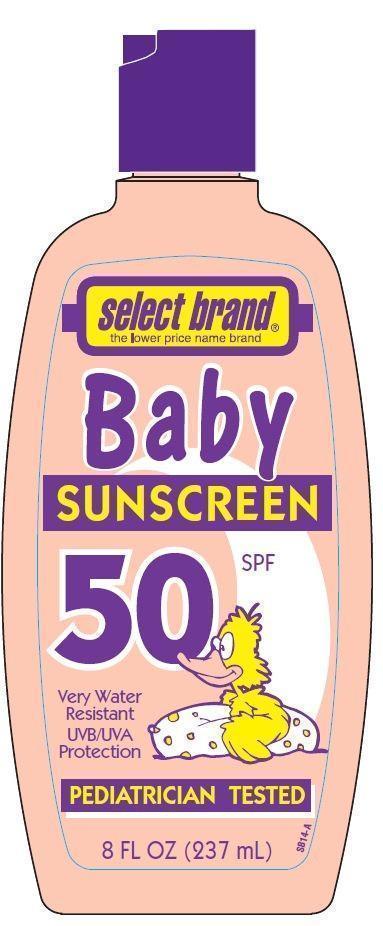 DRUG LABEL: Select Brand Baby Sunscreen
                
                
NDC: 15127-004 | Form: LOTION
Manufacturer: Select Brand Distributors
Category: otc | Type: HUMAN OTC DRUG LABEL
Date: 20121120

ACTIVE INGREDIENTS: AVOBENZONE 3 g/100 g; HOMOSALATE 13 g/100 g; OCTISALATE 5 g/100 g; OCTOCRYLENE 7 g/100 g; OXYBENZONE 4 g/100 g
INACTIVE INGREDIENTS: WATER; SORBITOL; STEARIC ACID; TROLAMINE; ALUMINUM STARCH OCTENYLSUCCINATE; BENZYL ALCOHOL; SORBITAN ISOSTEARATE; DIMETHICONE; METHYLPARABEN; TOCOPHEROL; PROPYLPARABEN; EDETATE DISODIUM

Drug Facts

Active ingredients

Avobenzone 3.0%
Homosalate 13.0%
Octisalate 5.0%
Octocrylene 7.0%
Oxybenzone 4.0%

Purpose

Sunscreen

Warnings

For external use only

When using this product

- keep out of eyes. Rinse with water to remove.

Stop use and ask a doctor if

- rash or irritation develops and lasts

KEEP OUT OF REACH OF CHILDREN

Keep out of each of children.If swallowed get medical help or contact a Poison Control Center right away.

Directions

- shake well
- apply generously and evenly before sun exposure and as needed
- children under 6 months of age: ask a doctor
- reapply frequently and after towel drying,swimming or perspiring

Other information

- may stain some materials

Inactive ingredients

Water, Sorbitol, Stearic Acid, Triethanolamine, Aluminum Starch Octenylsuccinate, Benzyl Alcohol, Sorbitan Isostearate, VP/Eicosene Copolymer, Dimethicone, Polyglyceryl-3 Distearate, Carbomer, Tocopherol, Disodium EDTA, Methylparaben, Propylparaben, Fragrance.

Principal Display Panel

select brand
the lower price name brand
Baby
SUNSCREEN
50 SPF
Very Water Resistant
UVB/UVA Protection
PEDIATRICIAN TESTED
8 FL OZ (237 mL)

Uses

- helps prevent sunburn
- higher SPF gives more sunburn protection
- retains SPF after 80 minutes of activity in the water